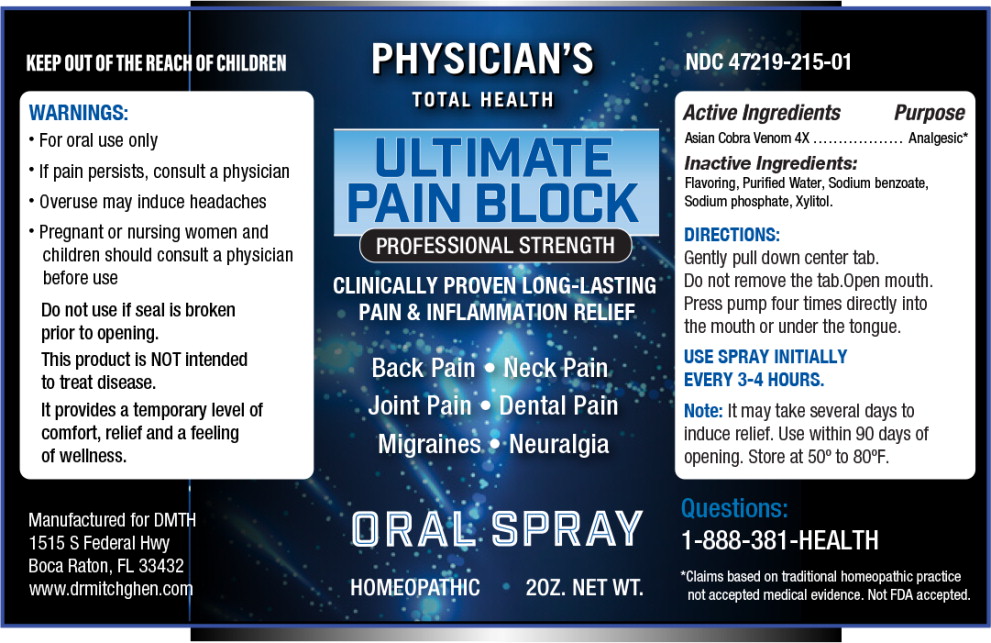 DRUG LABEL: Ultimate Pain Block
NDC: 47219-215 | Form: SPRAY, METERED
Manufacturer: Nutra Pharma Corporation
Category: homeopathic | Type: HUMAN OTC DRUG LABEL
Date: 20251104

ACTIVE INGREDIENTS: NAJA NAJA VENOM 4 [hp_X]/1 mL
INACTIVE INGREDIENTS: WATER; SODIUM BENZOATE; SODIUM PHOSPHATE; XYLITOL

DRUG FACTS

Active Ingredients

Asian Cobra Venom 4X

Purpose

Analgesic*

*Claims based on traditional homeopathic practice not accepted medical evidence. Not FDA accepted.

Inactive Ingredients:

Flavoring, Purified Water, Sodium benzoate, Sodium phosphate, Xylitol.

DIRECTIONS:

Gently pull down center tab.

Do not remove the tab. Open mouth.

Press pump four times directly into the mouth or under the tongue.

INDICATIONS AND USAGE

USE SPRAY INITIALLY EVERY 3-4 HOURS.

Note:It may take several days to induce relief. Use within 90 days of opening. Store at 50º to 80ºF.

WARNINGS:

- For oral use only
- If pain persists, consult a physician
- Overuse may induce headaches

PREGNANCY OR BREAST FEEDING

- Pregnant or nursing women and children should consult a physician before use

Do not use if seal is broken prior to opening.

This product is NOT intended to treat disease.

It provides a temporary level of comfort, relief and a feeling of wellness.

Questions:

1-888-381-HEALTH

Principal Display Panel - 2 oz Bottle Label

PHYSICIAN'S
TOTAL HEALTH

ULTIMATE
PAIN BLOCK

PROFESSIONAL STRENGTH

CLINICALLY PROVEN LONG-LASTING
PAIN & INFLAMMATION RELIEF

Back Pain • Neck Pain
Joint Pain • Dental Pain
Migraines • Neuralgia

ORAL SPRAY

HOMEOPATHIC

2OZ. NET WT.